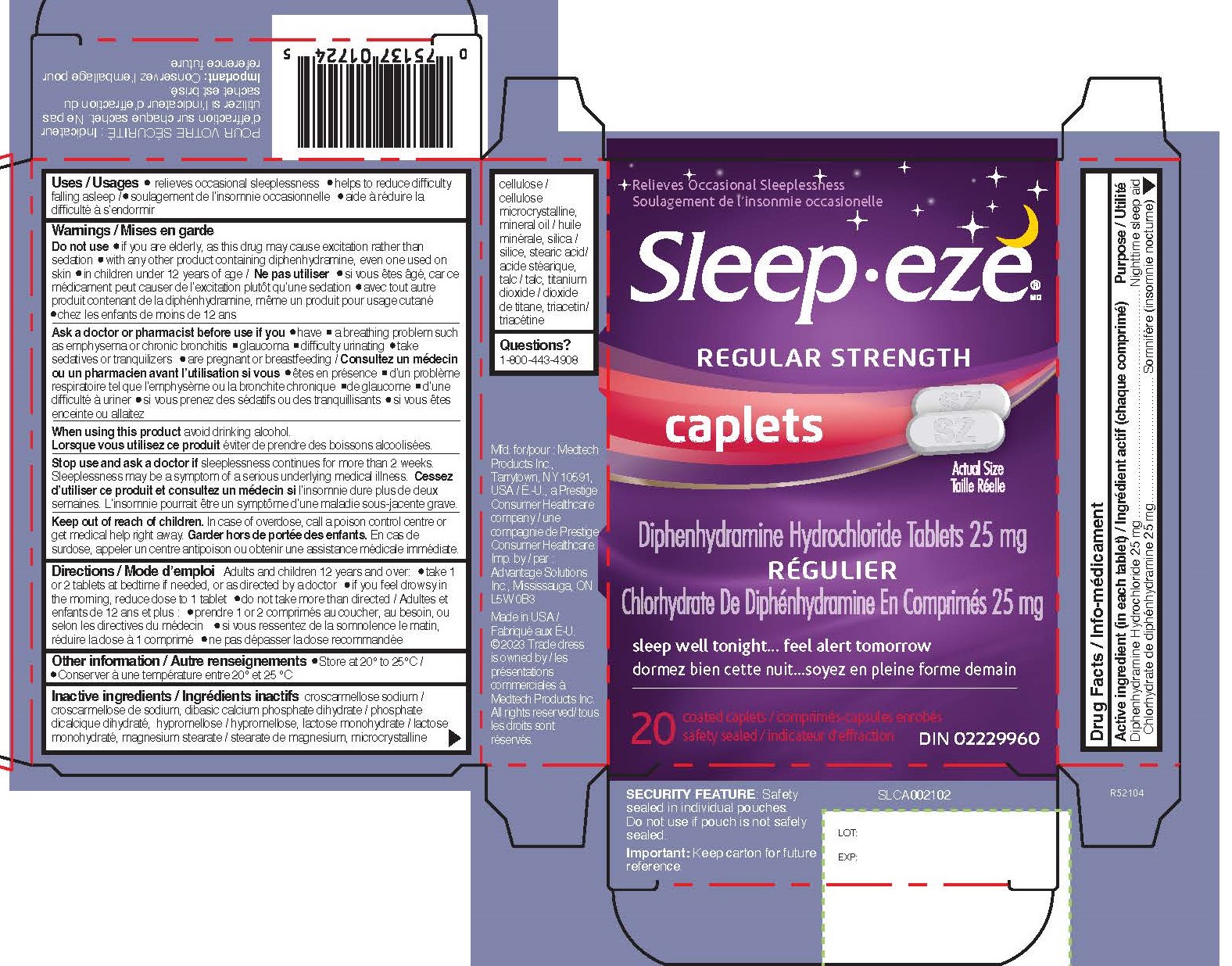 DRUG LABEL: Diphenhydramine Hydrochloride
NDC: 10267-4658 | Form: TABLET, FILM COATED
Manufacturer: Contract Pharmacal Corp.
Category: otc | Type: HUMAN OTC DRUG LABEL
Date: 20231130

ACTIVE INGREDIENTS: DIPHENHYDRAMINE HYDROCHLORIDE 25 mg/1 1
INACTIVE INGREDIENTS: DIBASIC CALCIUM PHOSPHATE DIHYDRATE; HYPROMELLOSES; LACTOSE MONOHYDRATE; MAGNESIUM STEARATE; SILICON DIOXIDE; STEARIC ACID; TALC; TITANIUM DIOXIDE; TRIACETIN; CROSCARMELLOSE SODIUM; LIGHT MINERAL OIL; MICROCRYSTALLINE CELLULOSE

4658- Export